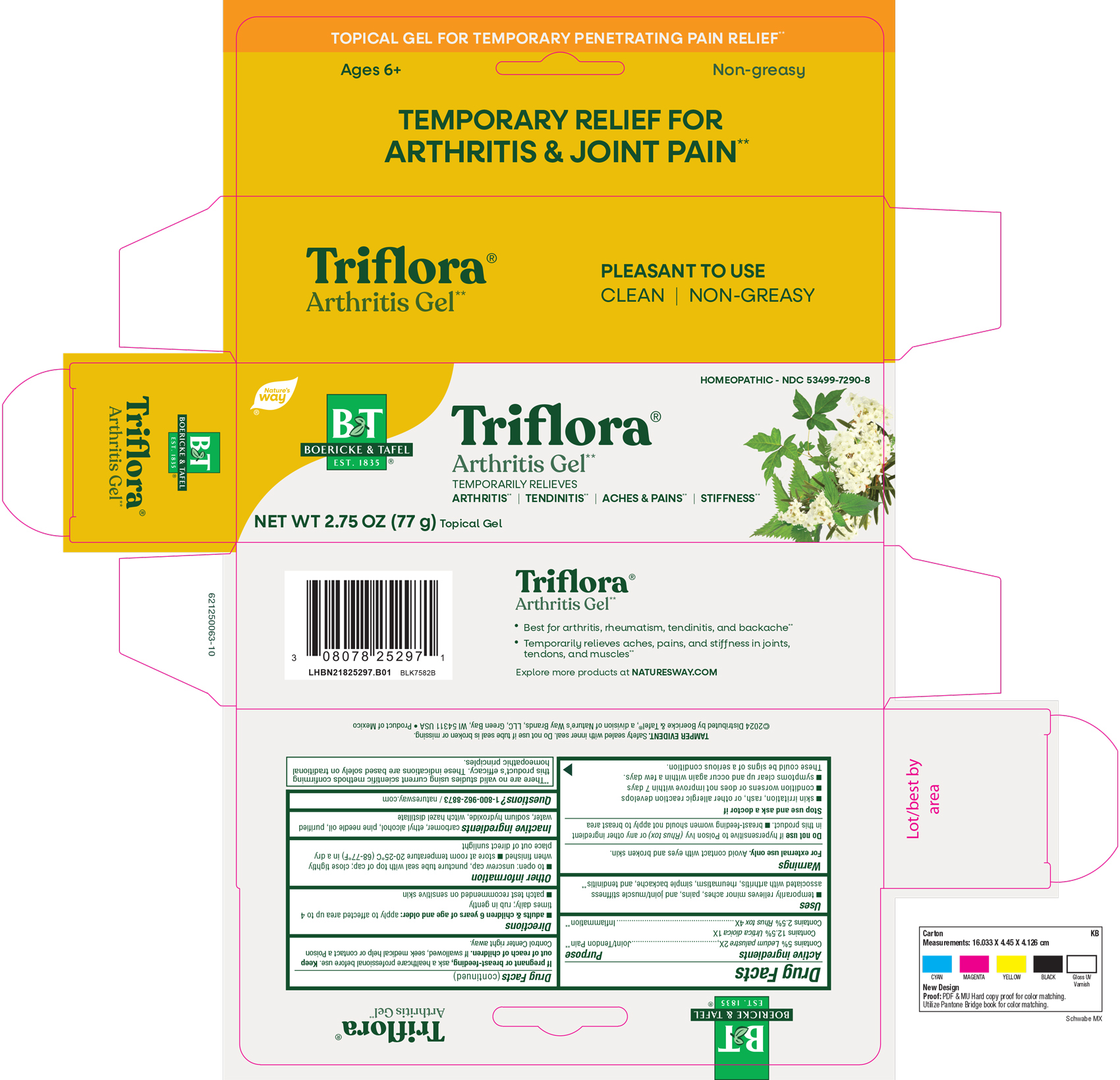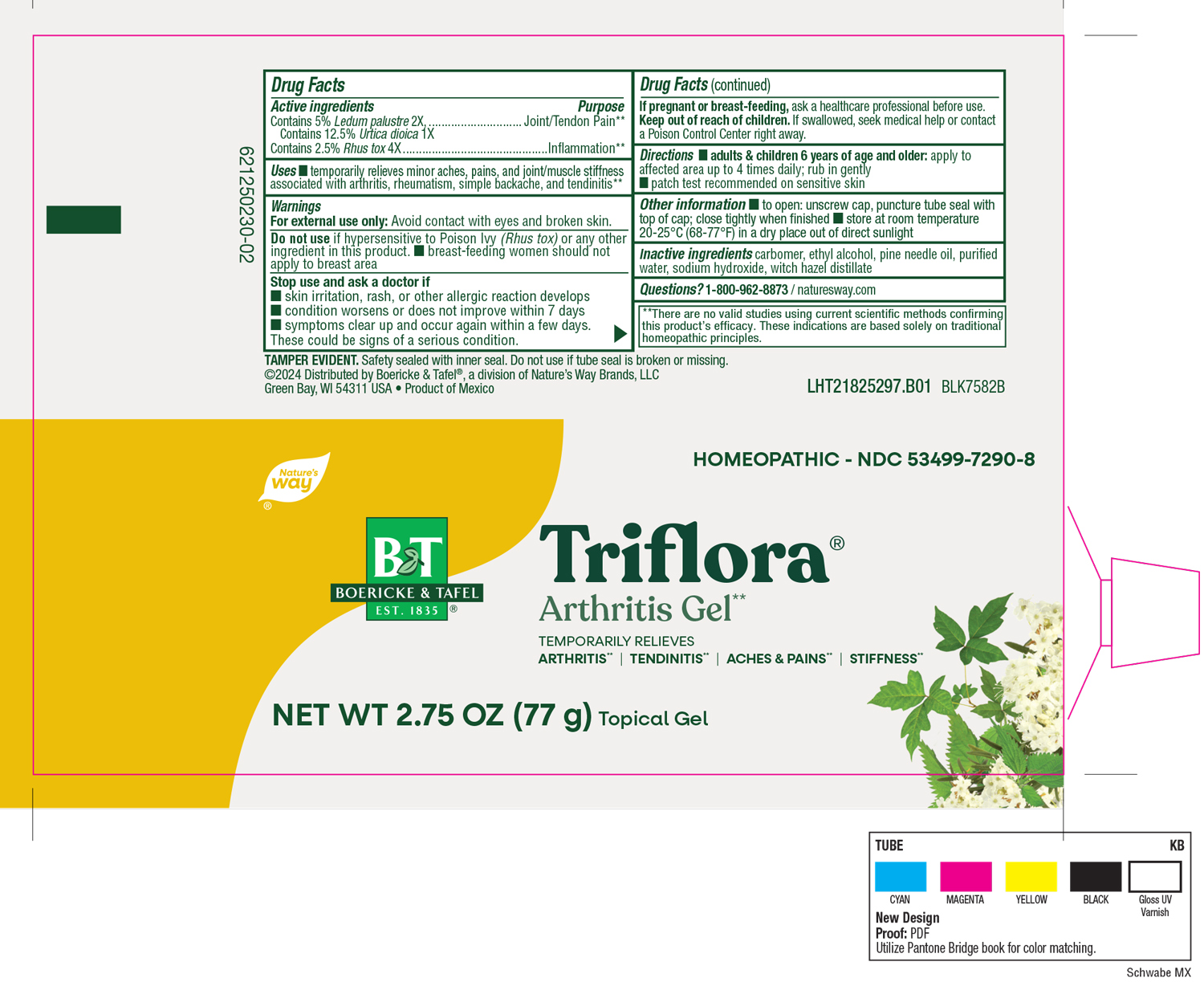 DRUG LABEL: Triflora Gel
NDC: 68466-2001 | Form: GEL
Manufacturer: Schwabe Mexico S.A. de C.V.
Category: homeopathic | Type: HUMAN OTC DRUG LABEL
Date: 20251118

ACTIVE INGREDIENTS: URTICA DIOICA 1 [hp_X]/77 g; TOXICODENDRON PUBESCENS LEAF 4 [hp_X]/77 g; LEDUM PALUSTRE TWIG 2 [hp_X]/77 g
INACTIVE INGREDIENTS: CARBOMER HOMOPOLYMER TYPE C; ALCOHOL; PINE NEEDLE OIL (PINUS SYLVESTRIS); WATER; SODIUM HYDROXIDE; WITCH HAZEL

Triflora Gel

Active Ingredients

Contains 5% Ledium palustre 2X

Contains 12.5% Urtica doica 1X

Contains 2.5 Rhus tox 4X

Inactive Ingredients

Carbomer

Ethyl Alcohol

Pine Needle Oil

Purified Water

Sodium Hydroxide

Witch Hazel Distillate

Dosage and Administration

Directions

Adult and children 6 years of age and older: apply to affected area up to 4 times daily; rub in gently.

Patch test recommended on sensitive skin.

Indications and Usage

Temporarily relieves minor aches, pains, and joint/muscle stiffness associated with arthritis, rheumatism, simple backache, and tendinitis.

Purpose

Temporarily relieves minor aches, pains, and joint/muscle stiffness associated with arthritis, rheumatism, simple backache, and tendinitis.

Warnings

For external use only. Avoid contact with eyes and broken skin.

Do not use if hypersensitive to Posion Ivy (Rhus tox) or any other ingredients in this product.

Breast-feeding women should not apply to breast area.

Stop Use

Stop use and ask a doctor if skin irritation, rash or other allergic reaction develops, condition worsens or does not improve within 7 days, symptoms clear up and occur again within a few days.

These could be signs of a serious condition.

Pregnancy or Breast Feeding

If pregnant or breast-feeding, ask a healthcare profressional before use.

Keep out of reach of children.

Overdosage

If swallowed, seek medical help or contact a Poison Control Center right away.